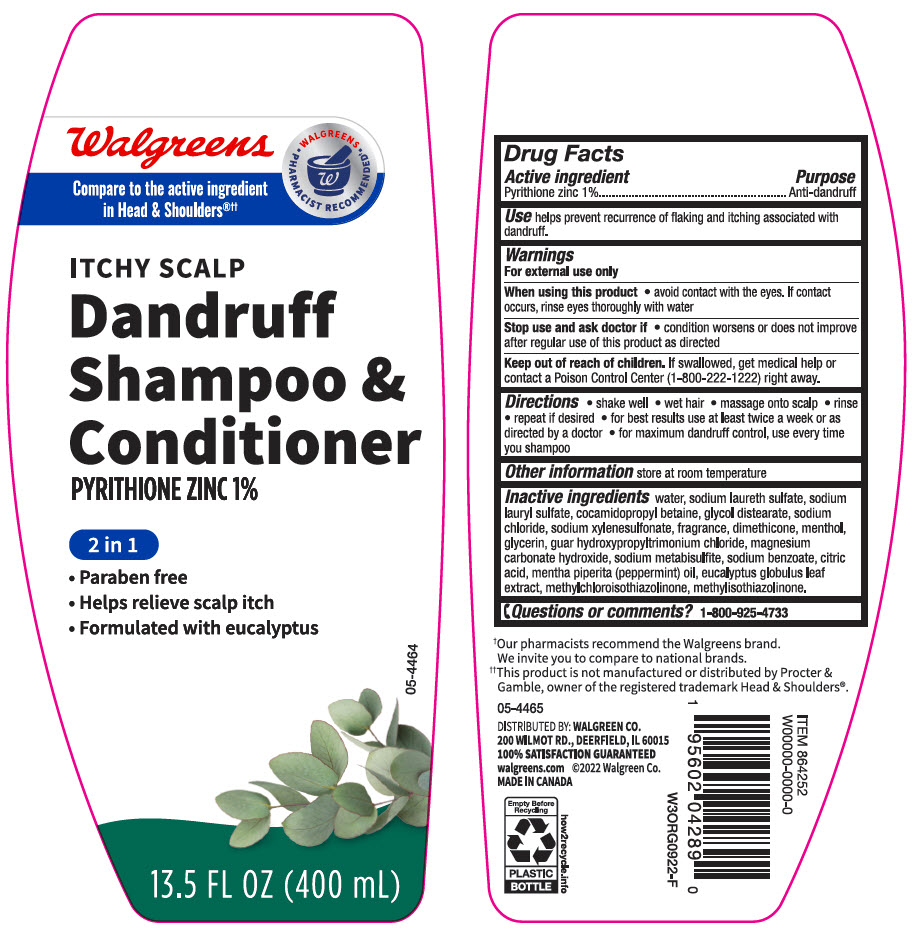 DRUG LABEL: Walgreens Dandruff Conditioner 2 in 1 Itchy Scalp
NDC: 0363-4289 | Form: SHAMPOO
Manufacturer: Walgreen Company
Category: otc | Type: HUMAN OTC DRUG LABEL
Date: 20241104

ACTIVE INGREDIENTS: Pyrithione Zinc 10 mg/1 mL
INACTIVE INGREDIENTS: Water; SODIUM LAURETH-3 SULFATE; Sodium Lauryl Sulfate; Cocamidopropyl Betaine; Glycol Distearate; Sodium Chloride; Sodium Xylenesulfonate; Dimethicone; MENTHOL, UNSPECIFIED FORM; Glycerin; GUAR HYDROXYPROPYLTRIMONIUM CHLORIDE; Magnesium Carbonate Hydroxide; SODIUM METABISULFITE; Sodium Benzoate; CITRIC ACID MONOHYDRATE; PEPPERMINT OIL; EUCALYPTUS GLOBULUS LEAF; Methylchloroisothiazolinone; Methylisothiazolinone

Walgreens Dandruff Shampoo & Conditioner 2 in 1 Itchy Scalp

Drug Facts

Active ingredient

Pyrithione Zinc 1%

Purpose

Anti-dandruff

Use

helps prevent recurrence of flaking and itching associated with dandruff.

Warnings

For external use only

When using this product

- avoid contact with the eyes. If contact occurs, rinse eyes thoroughly with water.

Stop use and ask a doctor if

- condition worsens or does not improve after regular use as directed.

Keep out of reach of children. If swallowed, get medical help or contact a Poison Control Center (1-800-222-1222) right away.

Directions

- shake well
- wet hair
- massage onto scalp
- rinse
- repeat if desired
- for best results use at least twice a week or as directed by a doctor
- for maximum dandruff control, use every time you shampoo

Other information

store at room temperature

Inactive ingredients

water, sodium laureth sulfate, sodium lauryl sulfate, cocamidopropyl betaine, glycol distearate, sodium chloride, sodium xylenesulfonate, fragrance, dimethicone, menthol, glycerin, guar hydroxypropyltrimonium chloride, magnesium carbonate hydroxide, sodium metabisulfite, sodium benzoate, citric acid, mentha piperita (peppermint) oil, eucalyptus globulus leaf extract, methylchloroisothiazolinone, methylisothiazolinone.

Questions or Comments?

1-800-925-4733

DISTRIBUTED BY: WALGREEN CO.
200 WILMOT RD., DEERFIELD, IL 60015

PRINCIPAL DISPLAY PANEL - 400 mL Bottle Label

Walgreens

Compare to the active ingredient
in Head & Shoulders®††

WALGREENS
• PHARMACIST RECOMMENDED†•

ITCHY SCALP
Dandruff
Shampoo &
Conditioner
PYRITHIONE ZINC 1%

2 in 1

- Paraben free
- Helps relieve scalp itch
- Formulated with eucalyptus

13.5 FL OZ (400 mL)

05-4464